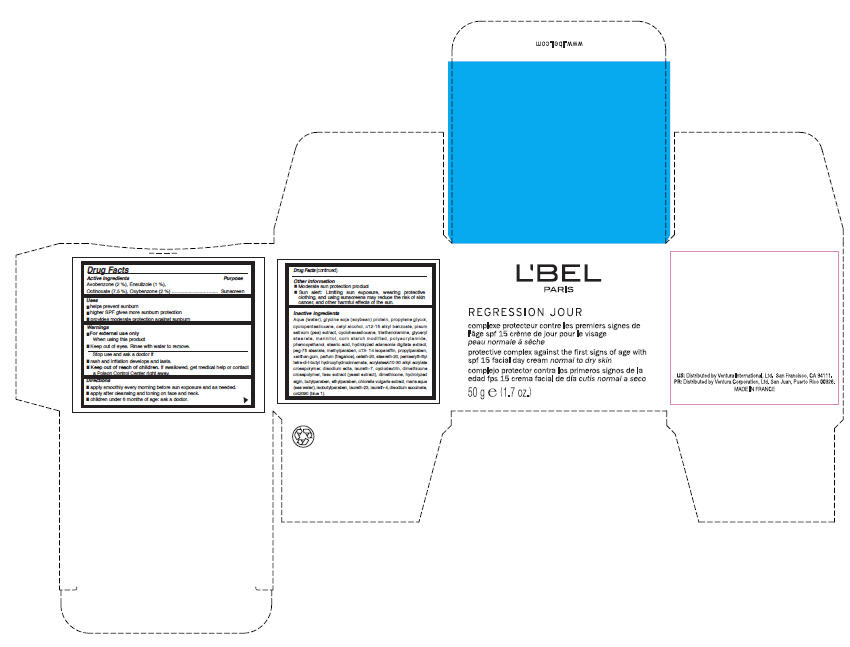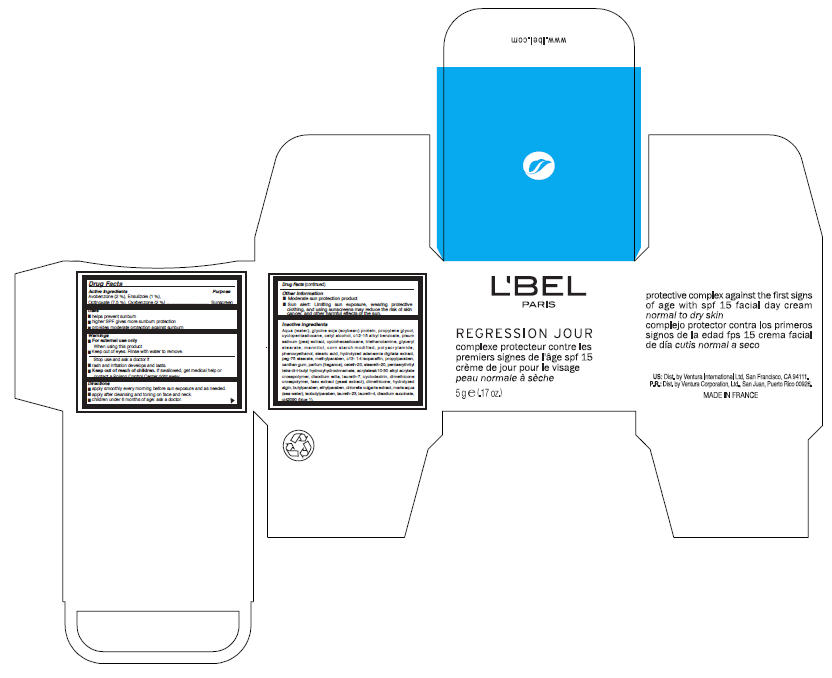 DRUG LABEL: LBel Paris 
NDC: 14783-049 | Form: CREAM
Manufacturer: Ventura International LTD
Category: otc | Type: HUMAN OTC DRUG LABEL
Date: 20100810

ACTIVE INGREDIENTS: Avobenzone 1 g/50 g; Ensulizole 0.5 g/50 g; Octinoxate 3.75 g/50 g; Oxybenzone 1 g/50 g
INACTIVE INGREDIENTS: water; soybean; propylene glycol; cyclomethicone 5; cetyl alcohol; c12-15 alkyl benzoate; snow pea; cyclomethicone 6; trolamine; glyceryl monostearate; mannitol; phenoxyethanol; stearic acid; methylparaben; c13-14 isoparaffin; propylparaben; xanthan gum; ceteth-20; steareth-20; edetate disodium; laureth-7; yeast; dimethicone; butylparaben; ethylparaben; isobutylparaben; laureth-23; laureth-4; sodium succinate anhydrous

L'BEL
PARIS
REGRESSION JOUR

Drug Facts

Active Ingredients

Avobenzone (2 %), Ensulizole (1 %), Octinoxate (7.5 %), Oxybenzone (2 %)

Purpose

Sunscreen

Uses

- helps prevent sunburn
- higher SPF gives more sunburn protection
- provides moderate protection against sunburn

Warnings

- For external use only.

When using this product

- keep out of eyes. Rinse with water to remove.

Stop use and ask a doctor if

- rash and irritation develops and lasts.

- Keep out of reach of children. If swallowed, get medical help or contact a Poison Control Center right away.

Directions

- apply smoothly every morning before sun exposure and as needed.
- apply after cleansing and toning on face and neck.
- children under 6 months of age: ask a doctor.

Other information

- Moderate sun protection product.
- Sun alert: Limiting sun exposure, wearing protective clothing, and using sunscreens may reduce the risk of skin cancer, and other harmful effects of the sun.

Inactive ingredients

Aqua (water), glycine soja (soybean) protein, propylene glycol, cyclopentasiloxane, cetyl alcohol, c12-15 alkyl benzoate, pisum sativum (pea) extract, cyclohexasiloxane, triethanolamine, glyceryl stearate, mannitol, corn starch modified, polyacrylamide, phenoxyethanol, stearic acid, hydrolyzed adansonia digitata extract, peg-75 stearate, methylparaben, c13- 14 isoparaffin, propylparaben, xanthan gum, parfum (fragance), ceteth-20, steareth-20, pentaerythrityl tetra-di-t-butyl hydroxyhydrocinnamate, acrylates/c10-30 alkyl acrylate crosspolymer, disodium edta, laureth-7, cyclodextrin, dimethicone crosspolymer, faex extract (yeast extract), dimethicone, hydrolyzed algin, butylparaben, ethylparaben, chlorella vulgaris extract, maris aqua (sea water), isobutylparaben, laureth-23, laureth-4, disodium succinate, ci42090 (blue 1).

PRINCIPAL DISPLAY PANEL - 50 g Jar Carton

L'BEL
PARIS

REGRESSION JOUR

protective complex against the first signs of age with
spf 15 facial day cream normal to dry skin

50 g e (1.7 oz.)

PRINCIPAL DISPLAY PANEL - 5 g Jar Carton

L'BEL
PARIS

REGRESSION JOUR

protective complex against the first signs
of age with spf 15 facial day cream
normal to dry skin

5 g e (.17 oz.)